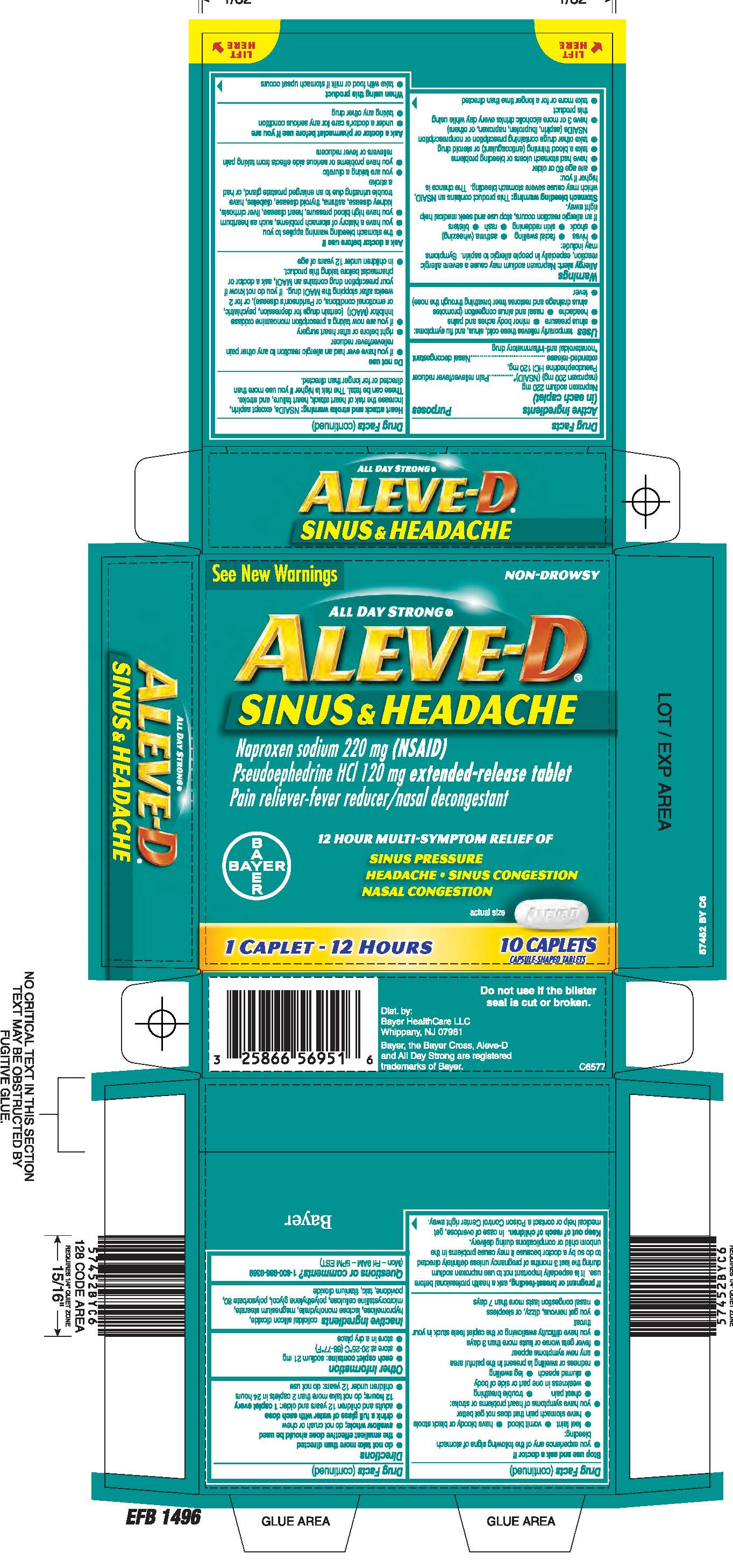 DRUG LABEL: Aleve-D Sinus and Headache
NDC: 0280-6045 | Form: TABLET
Manufacturer: Bayer HealthCare LLC.
Category: otc | Type: HUMAN OTC DRUG LABEL
Date: 20251204

ACTIVE INGREDIENTS: NAPROXEN SODIUM 220 mg/1 1; PSEUDOEPHEDRINE HYDROCHLORIDE 120 mg/1 1
INACTIVE INGREDIENTS: HYPROMELLOSES; LACTOSE MONOHYDRATE; SILICON DIOXIDE; MAGNESIUM STEARATE; MICROCRYSTALLINE CELLULOSE; POLYETHYLENE GLYCOL, UNSPECIFIED; POLYSORBATE 80; POVIDONE; TALC; TITANIUM DIOXIDE

Aleve-D Sinus & Headache

Drug Facts

Active ingredients

(in each caplet)

Naproxen sodium 220 mg

(naproxen 200 mg) (NSAID)*

Pseudoephedrine HCl 120 mg,

*nonsteroidal anti-inflammatory drug

Purposes

Pain reliever/fever reducer

Nasal decongestant

INDICATIONS AND USAGE

Uses temporarily relieves these cold, sinus, and flu symptoms: • sinus pressure • minor body aches and pains • headache • nasal and sinus congestion (promotes

sinus drainage and restores freer breathing through the nose) • fever

Warnings

Allergy alert: Naproxen sodium may cause a severe allergic

reaction, especially in people allergic to aspirin. Symptoms

may include: • hives • facial swelling • asthma (wheezing) • shock • skin reddening • rash • blisters

If an allergic reaction occurs, stop use and seek medical help

right away.

Stomach bleeding warning: This product contains an NSAID,

which may cause severe stomach bleeding. The chance is

higher if you: • are age 60 or older • have had stomach ulcers or bleeding problems • take a blood thinning (anticoagulant) or steroid drug • take other drugs containing prescription or nonprescription

NSAIDs (aspirin, ibuprofen, naproxen, or others) • have 3 or more alcoholic drinks every day while using

this product • take more or for a longer time than directed

Heart attack and stroke warning: NSAIDs, except aspirin, increase the risk of heart attack, heart failure, and stroke. These can be fatal. The risk is higher if you use more than directed or for longer than directed.

Do not use

• if you have ever had an allergic reaction to any other pain

reliever/fever reducer

• right before or after heart surgery

• if you are now taking a prescription monoamine oxidase

inhibitor (MAOI) (certain drugs for depression, psychiatric,

or emotional conditions, or Parkinson’s disease), or for 2

weeks after stopping the MAOI drug. If you do not know if

your prescription drug contains an MAOI, ask a doctor or

pharmacist before taking this product.

• in children under 12 years of age

Ask a doctor before use if

• the stomach bleeding warning applies to you

• you have a history of stomach problems, such as heartburn

• you have high blood pressure, heart disease, liver cirrhosis,

or kidney disease,asthma • thyroid disease, diabetes, have trouble urinating due to an enlarged prostate gland or had a stroke

• you are taking a diuretic

• you have problems or serious side effects from taking pain

relievers or fever reducers

Ask a doctor or pharmacist before use if you are

• under a doctor’s care for any serious condition

• taking any other drug

When using this product

• take with food or milk if stomach upset occurs

Stop use and ask a doctor if

● you experience any of the following signs of stomach

bleeding:

● feel faint • vomit blood • have bloody or black stools

● have stomach pain that does not get better

●you have symptoms of heart problems or stroke:

● chest pain

● trouble breathing

● weakness in one part or side of body

● slurred speech

● leg swelling

● redness or swelling is present in the painful area

● any new symptoms appear

● fever gets worse or lasts more than 3 days

● you have difficulty swallowing or the caplet feels stuck in your

throat

● you get nervous, dizzy, or sleepless

● nasal congestion lasts more than 7 days

PREGNANCY OR BREAST FEEDING

If pregnant or breast-feeding, ask a health professional before

use. It is especially important not to use naproxen sodium

during the last 3 months of pregnancy unless definitely directed

to do so by a doctor because it may cause problems in the

unborn child or complications during delivery.

Keep out of reach of children. In case of overdose, get

medical help or contact a Poison Control Center right away.

Directions

• do not take more than directed

• the smallest effective dose should be used

• swallow whole; do not crush or chew • drink a full glass of water with each dose

• adults and children 12 years and older: 1 caplet every

12 hours; do not take more than 2 caplets in 24 hours • children under 12 years: do not use

Other Information

• each caplet contains: sodium 21 mg • store at 20-25°C (68-77°F) • store in a dry place

Inactive ingredients colloidal silicon dioxide,

hypromellose, lactose monohydrate, magnesium stearate,

microcrystalline cellulose, polyethylene glycol, polysorbate 80,

povidone, talc, titanium dioxide

Questions or comments?

1-800-986-0369

(Mon – Fri 9AM – 5PM EST)

PACKAGE LABEL

See New Warnings

NON-DROWSY

ALL DAY STRONG®

ALEVE-D®

SINUS & HEADACHE

Naproxen sodium 220 mg (NSAID)

Pseudoephedrine HCl 120 mg extended-release tablets

Pain reliever-fever reducer/nasal decongestant

12 HOUR MULTI-SYMPTOM RELIEF OF

SINUS PRESSURE

HEADACE · SINUS CONGESTION

NASAL CONGESTION

actual size

1 CAPLET - 12 HOURS

10 CAPLETS

CAPSULE-SHAPED TABLETS